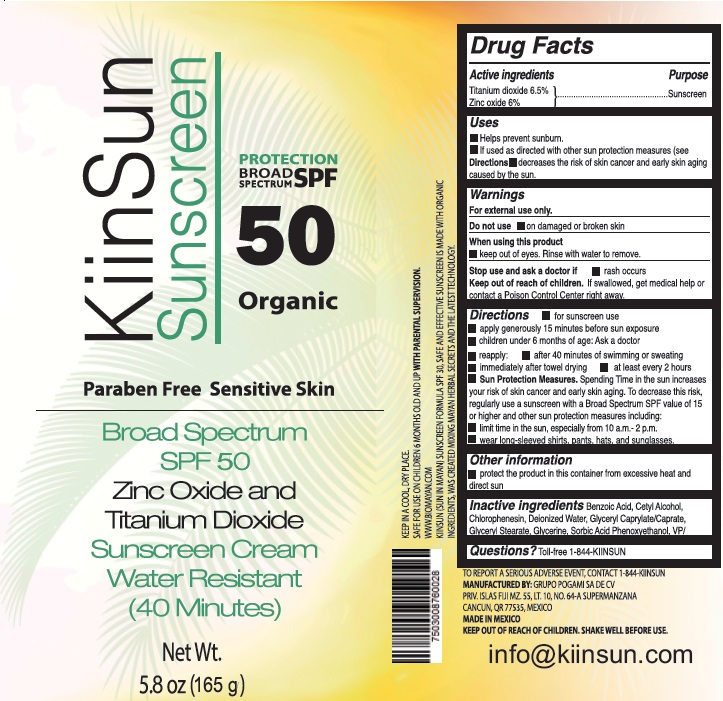 DRUG LABEL: KiinSun Sunscreen Broad Spectrum SPF50
NDC: 72431-001 | Form: CREAM
Manufacturer: Grupo Pogami, S.A. de C.V.
Category: otc | Type: HUMAN OTC DRUG LABEL
Date: 20200603

ACTIVE INGREDIENTS: TITANIUM DIOXIDE 65 mg/1 g; ZINC OXIDE 60 mg/1 g
INACTIVE INGREDIENTS: BENZOIC ACID; CETYL ALCOHOL; CHLORPHENESIN; WATER; GLYCERYL CAPRYLATE/CAPRATE; GLYCERYL MONOSTEARATE; GLYCERIN; SORBIC ACID; PHENOXYETHANOL

KiinSun Sunscreen Broad Spectrum SPF50

Active ingredients

Titanium dioxide 6.5%

Zinc oxide 6%

Purpose

Sunscreen

Uses

- Helps prevent sunburn.
- If used as directed with other sun protection measures (see Directions), decreases the risk of skin cancer and early skin aging caused by the sun.

Warnings

For external use only.

Do not use

- on damaged or broken skin

When using this product

- keep out of eyes. Rinse with water to remove.

Stop use and ask a doctor if

- rash occurs

Keep out of reach of children.

If swallowed, get medical help or contact a Poison Control Center right away.

Directions

- for sunscreen use
- apply generously 15 minutes before sun exposure
- children under 6 months of age: Ask a doctor
- reapply:
- after 40 minutes of swimming or sweating
- immediately after towel drying
- at least every 2 hours
- Sun Protection Measures. Spending Time in the sun increases your risk of skin cancer and early skin aging. To decrease this risk, regularly use a sunscreen with a Broad Spectrum SPF value of 15 or higher and other sun protection measures including:
- limit time in the sun, especially from 10 a.m.- 2 p.m.
- wear long-sleeved shirts, pants, hats, and sunglasses.

Other information

- protect the product in this container from excessive heat and direct sun

Inactive ingredients

Benzoic Acid, Cetyl Alcohol, Chlorophenesin, Deionized Water, Glyceryl Caprylate/Caprate, Glyceryl Stearate, Glycerine, Sorbic Acid Phenoxyethanol, VP/

Questions?

Toll-free 1-844-KIINSUN